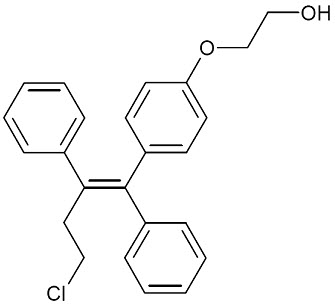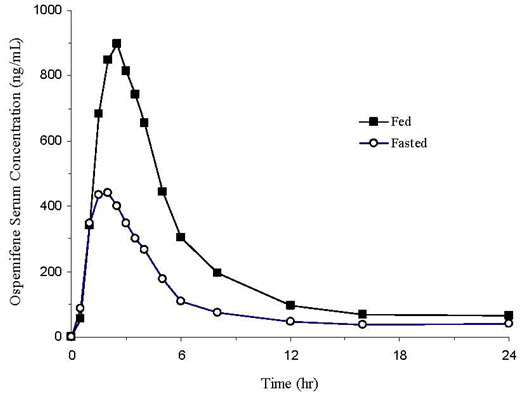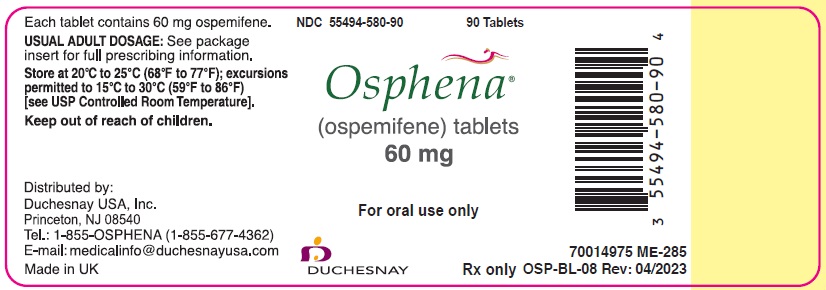 DRUG LABEL: Osphena
NDC: 55494-580 | Form: TABLET, FILM COATED
Manufacturer: Duchesnay USA, Inc.
Category: prescription | Type: HUMAN PRESCRIPTION DRUG LABEL
Date: 20250214

ACTIVE INGREDIENTS: OSPEMIFENE 60 mg/1 1
INACTIVE INGREDIENTS: SILICON DIOXIDE; HYPROMELLOSE, UNSPECIFIED; LACTOSE MONOHYDRATE; MAGNESIUM STEARATE; MANNITOL; MICROCRYSTALLINE CELLULOSE; POLYETHYLENE GLYCOL, UNSPECIFIED; POVIDONE, UNSPECIFIED; TITANIUM DIOXIDE; TRIACETIN; STARCH, CORN; SODIUM STARCH GLYCOLATE TYPE A POTATO

HIGHLIGHTS OF PRESCRIBING INFORMATION

These highlights do not include all the information needed to use OSPHENA safely and effectively. See full prescribing information for OSPHENA.
OSPHENA®(ospemifene) tablets, for oral use
Initial U.S. Approval: 2013

WARNING: ENDOMETRIAL CANCER and CARDIOVASCULAR DISORDERS

See full prescribing information for complete boxed warning.

OSPHENA is an estrogen agonist/antagonist with tissue selective effects. In the endometrium, OSPHENA has estrogen agonistic effects. There is an increased risk of endometrial cancer in a woman with a uterus who uses unopposed estrogens. Perform adequate diagnostic measures, including directed and random endometrial sampling when indicated, to rule out malignancy in postmenopausal women with undiagnosed persistent or recurring abnormal genital bleeding [see Warnings and Precautions (5.2)].

Estrogen-alone therapy has an increased risk of stroke and deep vein thrombosis (DVT). OSPHENA 60 mg had cerebral thromboembolic and hemorrhagic stroke incidence rates of 1.13 and 3.39 per thousand women years, respectively vs. 3.15 and 0 per thousand women years, respectively with placebo. For deep vein thrombosis, the incidence rate for OSPHENA 60 mg is 2.26 per thousand women years (2 reported cases) vs. 3.15 per thousand women years (1 reported case) with placebo [see Warnings and Precautions (5.1)].

RECENT MAJOR CHANGES

Warnings and Precautions, Malignant Neoplasms (5.2) 02/2025

1 INDICATIONS AND USAGE

OSPHENA is an estrogen agonist/antagonist indicated for:

- The treatment of moderate to severe dyspareunia, a symptom of vulvar and vaginal atrophy, due to menopause. (1.1)
- The treatment of moderate to severe vaginal dryness, a symptom of vulvar and vaginal atrophy, due to menopause. (1.2)

2 DOSAGE AND ADMINISTRATION

- One tablet taken orally once daily with food. (2.1, 2.2)

3 DOSAGE FORMS AND STRENGTHS

Tablet: 60 mg (3)

4 CONTRAINDICATIONS

- Undiagnosed abnormal genital bleeding (4)
- Estrogen-dependent neoplasia (4, 5.2)
- Active DVT, pulmonary embolism (PE), or a history of these conditions (4, 5.1)
- Active arterial thromboembolic disease (for example, stroke and myocardial infarction [MI]), or a history of these conditions (4, 5.1)
- Hypersensitivity (for example, angioedema, urticaria, rash, pruritus) to OSPHENA or any ingredients (4)
- Known or suspected pregnancy (4, 8.1)

5 WARNINGS AND PRECAUTIONS

- Venous Thromboembolism: Risk of DVT and PE (5.1)
- Known, suspected, or history of breast cancer (5.2)
- Severe Hepatic Impairment (5.3, 8.7, 12.3)

6 ADVERSE REACTIONS

The most common adverse reactions (≥1 percent) with OSPHENA are: hot flush, vaginal discharge, muscle spasms, headache, hyperhidrosis, vaginal hemorrhage, night sweats. (6.1)

To report SUSPECTED ADVERSE REACTIONS, contact Duchesnay Inc. at 1-855-OSPHENA (1-855-677-4362) or FDA at 1-800-FDA-1088 or www.fda.gov/medwatch.

7 DRUG INTERACTIONS

- Do not use estrogens or estrogen agonist/antagonist concomitantly with OSPHENA. (7.1, 12.3)
- Do not use fluconazole concomitantly with OSPHENA. Fluconazole increases serum concentrations of OSPHENA. (7.2, 12.3)
- Do not use rifampin concomitantly with OSPHENA. Rifampin decreases serum concentration of OSPHENA. (7.2, 12.3)

FULL PRESCRIBING INFORMATION

WARNING: ENDOMETRIAL CANCER and CARDIOVASCULAR DISORDERS

Endometrial Cancer

OSPHENA is an estrogen agonist/antagonist with tissue selective effects. In the endometrium, OSPHENA has estrogen agonistic effects. There is an increased risk of endometrial cancer in a woman with a uterus who uses unopposed estrogens. Perform adequate diagnostic measures, including directed and random endometrial sampling when indicated, to rule out malignancy in postmenopausal women with undiagnosed persistent or recurring abnormal genital bleeding [see Warnings and Precautions (5.2)].

Cardiovascular Disorders

In the clinical trials for OSPHENA (duration of treatment up to 15 months), the incidence rates of thromboembolic and hemorrhagic stroke were 1.13 and 3.39 per thousand women years, respectively in the OSPHENA 60 mg treatment group and 3.15 and 0 with placebo [see Warnings and Precautions (5.1)]. The incidence of DVT was 2.26 per thousand women years (2 reported cases) in the OSPHENA 60 mg treatment group and 3.15 per thousand women years (1 reported case) with placebo [see Warnings and Precautions (5.1)]. OSPHENA should be prescribed for the shortest duration consistent with treatment goals and risks for the individual woman.

Increased risks of stroke and deep vein thrombosis (DVT) are reported in postmenopausal women (50 to 79 years of age) during 7.1 years of treatment with daily oral conjugated estrogens (CE) [0.625 mg]-alone, relative to placebo as part of the Women's Health Initiative (WHI) [see Warnings and Precautions (5.1)].

1 INDICATIONS AND USAGE

OSPHENA is indicated for:

2 DOSAGE AND ADMINISTRATION

OSPHENA is an estrogen agonist/antagonist which has agonistic effects on the endometrium [see Warnings and Precautions (5.2)].

Use OSPHENA for the shortest duration consistent with treatment goals and risks for the individual woman. Reevaluate postmenopausal women periodically as clinically appropriate to determine if treatment is still necessary.

2.1 Treatment of Moderate to Severe Dyspareunia, a Symptom of Vulvar and Vaginal Atrophy, Due to Menopause

One 60 mg tablet taken orally with food once daily.

2.2 Treatment of Moderate to Severe Vaginal Dryness, a Symptom of Vulvar and Vaginal Atrophy, Due to Menopause

One 60 mg tablet taken orally with food once daily.

3 DOSAGE FORMS AND STRENGTHS

OSPHENA tablets are white to off-white, oval, biconvex, film coated tablets containing 60 mg of ospemifene and engraved with "60" on one side.

4 CONTRAINDICATIONS

OSPHENA is contraindicated in women with any of the following conditions:

- Undiagnosed abnormal genital bleeding.
- Estrogen-dependent neoplasia.
- Active DVT, PE, or a history of these conditions.
- Active arterial thromboembolic disease (for example, stroke and MI), or a history of these conditions.
- Hypersensitivity (for example, angioedema, urticaria, rash, pruritus) to OSPHENA or any ingredients.
- OSPHENA is contraindicated in women who are or may become pregnant. OSPHENA may cause fetal harm when administered to a pregnant woman. Ospemifene was embryo-fetal lethal with labor difficulties and increased pup deaths in rats at doses below clinical exposures, and embryo-fetal lethal in rabbits at 10 times the clinical exposure based on mg/m^2. If this drug is used during pregnancy, or if a woman becomes pregnant while taking this drug, she should be apprised of the potential hazard to a fetus.

5 WARNINGS AND PRECAUTIONS

5.1 Cardiovascular Disorders

Manage appropriately any risk factors for cardiovascular disorders, arterial vascular disease (for example, hypertension, diabetes mellitus, tobacco use, hypercholesterolemia, and obesity) and/or venous thromboembolism (VTE) (for example, personal history or family history of VTE, obesity, and systemic lupus erythematosus).

Stroke

In the clinical trials for OSPHENA (duration of treatment up to 15 months), the incidence rates of thromboembolic and hemorrhagic stroke were 1.13 and 3.39 per thousand women years, respectively in OSPHENA 60 mg treatment group and 3.15 and 0 per thousand women years in placebo.

Immediately discontinue OSPHENA if a thromboembolic or hemorrhagic stroke occurs or is suspected.

The WHI estrogen-alone substudy reported a statistically significant increased risk of stroke in women 50 to 79 years of age receiving daily CE (0.625 mg)-alone compared to women in the same age group receiving placebo (45 versus 33 strokes per ten thousand women years, respectively). The increase in risk was demonstrated in year 1 and persisted.

Coronary Heart Disease

Two cases of myocardial infarction (MI) occurred in women receiving 60 mg of ospemifene in the OSPHENA clinical trials.

The WHI estrogen-alone substudy reported no overall effect on coronary heart disease (CHD) events (defined as nonfatal MI, silent MI, or CHD death) in women receiving estrogen-alone compared to placebo.

Venous Thromboembolism

Two cases of DVT occurred in women receiving OSPHENA 60 mg in the OSPHENA clinical trials. Immediately discontinue OSPHENA if a VTE occurs or is suspected.

If feasible, discontinue OSPHENA at least 4 to 6 weeks before surgery of the type associated with an increased risk of thromboembolism, or during periods of prolonged immobilization.

In the WHI estrogen-alone substudy, the risk of VTE (DVT and PE) was increased for women receiving daily CE (0.625 mg)-alone compared to placebo (30 versus 22 per ten thousand women years), although only the increased risk of DVT reached statistical significance (23 versus 15 per ten thousand women years). The increase in VTE risk was demonstrated during the first 2 years.

5.2 Malignant Neoplasms

Endometrial Cancer

OSPHENA is an estrogen agonist/antagonist with tissue selective effects. In the endometrium, OSPHENA has agonistic effects. In the OSPHENA clinical trials (60 mg treatment group), no cases of endometrial cancer were seen with exposure up to 52 weeks. There was a single case of simple hyperplasia without atypia. Endometrial thickening equal to 5 mm or greater was seen in the OSPHENA up to 52 weeks treatment groups at a rate of 101.4 per thousand women vs. 20.9 per thousand women for placebo. The incidence of any type of proliferative (weakly plus active plus disordered) endometrium was 26.3 per thousand women in the OSPHENA up to 52 weeks treatment groups vs. 0 per thousand women for placebo. Uterine polyps occurred at an incidence of 19.6 per thousand women in the OSPHENA up to 52 weeks treatment groups vs. 8.3 per thousand women for placebo.

An increased risk of endometrial cancer has been reported with the use of unopposed estrogen therapy in a woman with a uterus. The reported endometrial cancer risk among unopposed estrogen users is about 2 to 12 times greater than in non-users, and appears dependent on duration of treatment and on estrogen dose. Most studies show no significant increased risk associated with the use of estrogens for less than 1 year. The greatest risk appears to be associated with prolonged use, with increased risks of 15- to 24-fold for 5 to 10 years or more. This risk has been shown to persist for at least 8 to 15 years after estrogen therapy is discontinued. Adding a progestin to postmenopausal estrogen therapy has been shown to reduce the risk of endometrial hyperplasia, which may be a precursor to endometrial cancer. There are, however, possible risks that may be associated with the use of progestins with estrogens compared to estrogen-alone regimens. These include an increased risk of breast cancer. The use of progestins with OSPHENA therapy was not evaluated in the clinical trials.

Clinical surveillance of all women using OSPHENA is important. Perform adequate diagnostic measures, including directed or random endometrial sampling when indicated, to rule out malignancy in postmenopausal women with undiagnosed persistent or recurring abnormal genital bleeding with unknown etiology.

Breast Cancer

OSPHENA 60 mg has not been adequately studied in women with breast cancer; therefore, it should not be used in women with known or suspected breast cancer or with a history of breast cancer.

The Women’s Health Initiative (WHI) substudy of daily conjugated estrogen (CE) (0.625 mg)-alone provided information about breast cancer in estrogen-alone users. In the WHI estrogen alone substudy, after an average follow-up of 7.1 years, daily CE alone was not associated with an increased risk of invasive breast cancer [relative risk (RR) 0.80] compared to placebo.

After a mean follow-up of 5.6 years, the WHI substudy of daily CE (0.625 mg) plus medroxyprogesterone acetate (MPA) (2.5 mg) reported an increased risk of invasive breast cancer in women who took daily CE plus MPA compared to placebo. In this substudy, prior use of estrogen-alone or estrogen plus progestin therapy was reported by 26 percent of the women. The relative risk of invasive breast cancer was 1.24 and the absolute risk was 41 versus 33 cases per 10,000 women-years, for CE plus MPA compared with placebo. Among women who reported prior use of hormone therapy, the relative risk of invasive breast cancer was 1.86, and the absolute risk was 46 versus 25 cases per 10,000 women-years, for CE plus MPA compared with placebo. Among women who reported no prior use of hormone therapy, the relative risk of invasive breast cancer was 1.09, and the absolute risk was 40 versus 36 cases per 10,000 women-years for CE plus MPA compared with placebo. In the same substudy, invasive breast cancers were larger, were more likely to be node positive, and were diagnosed at a more advanced stage in the CE (0.625 mg) plus MPA (2.5 mg) group compared with the placebo group. Metastatic disease was rare, with no apparent difference between the two groups. Other prognostic factors, such as histologic subtype, grade and hormone receptor status did not differ between the groups.

Consistent with the Women’s Health Initiative (WHI) clinical trials, observational studies have also reported an increased risk of breast cancer for estrogen plus progestin therapy and a smaller, but still increased, risk for estrogen-alone therapy after several years of use. One large meta-analysis of prospective cohort studies reported increased risks that were dependent upon duration of use and could last up to >10 years after discontinuation of estrogen plus progestin therapy and estrogen-alone therapy. Extension of the WHI trials also demonstrated increased breast cancer risk associated with estrogen plus progestin therapy. Observational studies also suggest that the risk of breast cancer was greater, and became apparent earlier, with estrogen plus progestin therapy as compared to the risk with estrogen-alone therapy. However, these studies have not found significant variation in the risk of breast cancer among different estrogen plus progestin combinations, doses, or routes of administration.

The use of estrogen-alone and estrogen plus progestin has been reported to result in an increase in abnormal mammograms requiring further evaluation.

All women should receive yearly breast examinations by a healthcare provider and perform monthly breast self-examinations. In addition, mammography examinations should be scheduled based on patient age, risk factors, and prior mammogram results.

5.3 Severe Hepatic Impairment

OSPHENA should not be used in women with severe hepatic impairment [see Use in Specific Populations (8.7), and Clinical Pharmacology (12.3)] .

6 ADVERSE REACTIONS

The following serious adverse reactions are discussed elsewhere in the labeling:

- Cardiovascular Disorders [see Boxed Warning, Warnings and Precautions (5.1)]
- Malignant Neoplasms [see Boxed Warning, Warnings and Precautions (5.2)]

6.1 Clinical Trials Experience

Because clinical trials are conducted under widely varying conditions, adverse reaction rates observed in the clinical trials of a drug cannot be directly compared to rates in the clinical trials of another drug and may not reflect the rates observed in practice.

The safety of OSPHENA has been assessed in ten phase 2/3 trials (N=2209) with doses ranging from 5 to 90 mg per day. The duration of treatment in these studies ranged from 6 weeks to 15 months. The majority of women (N=1683) had treatment exposure up to 12 weeks; 847 had up to 52 weeks (1 year) of exposure.

The incidence rates of thromboembolic and hemorrhagic stroke were 1.13 per thousand women years (1 reported case of thromboembolic stroke) and 3.39 per thousand women years (3 reported cases of hemorrhagic stroke), respectively in OSPHENA 60 mg treatment group and 3.15 (1 case of thromboembolic stroke) and 0 per thousand women years, respectively in placebo. There were 2 reported cases of DVT among the 1459 women in the OSPHENA 60 mg treatment group and 1 case of DVT among the 1136 women in the placebo group.

Table 1 lists adverse reactions occurring more frequently in the OSPHENA 60 mg treatment group than in placebo and at a frequency ≥1% in the 12-week, double-blind, placebo-controlled clinical trials. Table 2 lists adverse reactions occurring more frequently in the OSPHENA 60 mg treatment group than in placebo and at a frequency ≥1% in all clinical trials up to 52-weeks.

Table 1: Adverse Reactions Reported More Commonly in the OSPHENA Treatment Group (60 mg Once Daily) and at Frequency ≥1.0% in the 12 Week Double-Blind, Controlled Clinical Trials with OSPHENA vs. Placebo
 | Ospemifene 60 mg (N=1459) % | Placebo (N=1136) %
Vascular Disorders
Hot flush | 6.5 | 2.6
Reproductive System and Breast Disorders
Vaginal discharge | 3.8 | 0.4
Musculoskeletal and Connective Tissue Disorders
Muscle spasms | 1.8 | 0.6
Skin and Subcutaneous Tissue Disorders
Hyperhidrosis | 1.1 | 0.2

Table 2: Adverse Reactions Reported More Commonly in the OSPHENA Treatment Group (60 mg Once Daily) and at Frequency ≥1.0% in All Clinical Trials up to 52 Weeks (Safety Population)
 | Ospemifene 60 mg All Trials (N=847) % | Placebo (N=165) %
Nervous System Disorders
Headaches | 2.8 | 2.4
Vascular Disorders
Hot flush | 12.2 | 4.2
Musculoskeletal and Connective Tissue Disorders
Muscle spasms | 4.5 | 2.4
Skin and Subcutaneous Tissue Disorders
Hyperhidrosis | 2.5 | 1.8
Night sweats | 1.2 | 0.0
Reproductive System and Breast Disorders
Vaginal discharge | 6.0 | 0.6
Vaginal hemorrhage | 1.3 | 0.0

6.2 Postmarketing Experience

The following adverse reactions have been identified during post-approval use of ospemifene. Because these reactions are reported voluntarily from a population of uncertain size, it is not possible to reliably estimate their frequency or establish a causal relationship to drug exposure.

Neoplasms Benign, Malignant and Unspecified (incl. cysts and polyps): endometrial hyperplasia, endometrial cancer

Immune System Disorders: allergic conditions including hypersensitivity, angioedema

Nervous System Disorders: headache

Vascular Disorders: deep vein thrombosis, thrombosis, pulmonary embolism

Skin and Subcutaneous Tissue Disorders: rash, rash erythematous, rash generalized, pruritus, urticaria

7 DRUG INTERACTIONS

OSPHENA is primarily metabolized by CYP3A4 and CYP2C9. CYP2C19 and other pathways contribute to the metabolism of ospemifene.

7.1 Estrogens and Estrogen Agonist/Antagonist

Do not use OSPHENA concomitantly with estrogens and estrogen agonists/antagonists. The safety of concomitant use of OSPHENA with estrogens and estrogen agonists/antagonists has not been studied.

7.2 Fluconazole

Do not use OSPHENA concomitantly with fluconazole, a moderate CYP3A / strong CYP2C9 / moderate CYP2C19 inhibitor. Fluconazole increases the systemic exposure of ospemifene by 2.7-fold. Administration of fluconazole with ospemifene may increase the risk of OSPHENA-related adverse reactions [see Clinical Pharmacology (12.3)] .

7.3 Rifampin

Rifampin, a strong CYP3A4 / moderate CYP2C9 / moderate CYP2C19 inducer, decreases the systemic exposure of ospemifene by 58%. Therefore, co-administration of OSPHENA with drugs such as rifampin which induce CYP3A4, CYP2C9 and/or CYP2C19 activity would be expected to decrease the systemic exposure of ospemifene, which may decrease the clinical effect [see Clinical Pharmacology (12.3)] .

7.4 Ketoconazole

Ketoconazole, a strong CYP3A4 inhibitor, increases the systemic exposure of ospemifene by 1.4-fold. Administration of ketoconazole chronically with ospemifene may increase the risk of OSPHENA-related adverse reactions [see Clinical Pharmacology (12.3)] .

7.5 Warfarin

Repeated administration of ospemifene had no effect on the pharmacokinetics of a single 10 mg dose of warfarin. No study was conducted with multiple doses of warfarin. The effect of ospemifene on clotting time such as the International Normalized Ratio (INR) or prothrombin time (PT) was not studied [see Clinical Pharmacology (12.3)] .

7.6 Highly Protein-Bound Drugs

Ospemifene is more than 99% bound to serum proteins and might affect the protein binding of other drugs. Use of OSPHENA with other drug products that are highly protein-bound may lead to increased exposure of either that drug or ospemifene [see Clinical Pharmacology (12.3)] .

7.7 Multiple Enzyme Inhibition

Co-administration of OSPHENA with a drug known to inhibit CYP3A4 and CYP2C9 isoenzymes may increase the risk of OSPHENA-related adverse reactions.

8 USE IN SPECIFIC POPULATIONS

8.1 Pregnancy

Risk Summary

Not Recommended During Pregnancy

OSPHENA is contraindicated in women who are or may become pregnant. If this drug is used during pregnancy, or if a woman becomes pregnant while taking this drug, she should be apprised of the potential hazard to a fetus [see Contraindications (4)].

Based on animal data, OSPHENA is likely to increase the risk of adverse outcomes during pregnancy and labor. Adverse findings at maternally toxic doses included embryofetal lethality in rats and rabbits, and neonatal mortality and difficult labor in rats. The reproductive effects observed are consistent with and are considered to be related to estrogen receptor activity of OSPHENA.

In the U.S. general population, the estimated background risk of major birth defects and miscarriage in clinically recognized pregnancies is 2% to 4% and 15% to 20%, respectively.

Data

Animal Data

The effects of ospemifene on embryo-fetal development were studied in rats (0.1, 1, or 4 mg/kg/day) and rabbits (3, 10, or 30 mg/kg/day) when treated from implantation through organogenesis [Gestation Day (GD) 6-16 in the rat and GD6-18 in the rabbit. In rabbits, there was an increase in the incidence of total resorptions at 30 mg/kg/day (10 times the human exposure based on body surface area mg/m^2)]. Drug-induced malformations were not observed in either rats or rabbits.

The effects of ospemifene on pre- and postnatal development were studied in pregnant rats (0.01, 0.05, and 0.25 mg/kg/day) treated from implantation (GD6) through lactation (Lactation Day (LD) 21). Pregnant rats given 0.05 or 0.25 mg/kg/day ospemifene (0.8% to 4% the human exposure based on body surface area mg/m^2) had a significantly prolonged and difficult gestation, increased post-implantation loss, increased number of dead pups at birth, and an increased incidence of postnatal loss. Ospemifene did not induce adverse effects in the surviving offspring of pregnant rats at drug exposures up to 4% the human exposure.

8.2 Lactation

Risk Summary

It is not known whether OSPHENA is excreted in human breast milk. There are no data on the effects of OSPHENA on the breastfed child or the effects on milk production. Ospemifene was excreted in rat milk [see Data].

The developmental and health benefits of breastfeeding should be considered along with the mother’s clinical need for OSPHENA and any potential adverse effects on the breastfed child from OSPHENA or from the underlying maternal condition.

Data

In a nonclinical study, ospemifene was excreted in rat milk and detected at concentrations higher than that in maternal plasma.

8.4 Pediatric Use

OSPHENA is not indicated in pediatric patients. Clinical studies have not been conducted in the pediatric population.

8.5 Geriatric Use

Of the 2209 OSPHENA-treated women enrolled in the ten phase 2/3 trials of OSPHENA, >19 percent were 65 years of age or older. No clinically meaningful differences in safety or effectiveness were observed between these women and younger women less than 65 years of age.

8.6 Renal Impairment

The pharmacokinetics of ospemifene in women with severe renal impairment (CrCL <30 mL/min) was similar to those in women with normal renal function [see Clinical Pharmacology (12.3)].

No dose adjustment of OSPHENA is required in women with renal impairment.

8.7 Hepatic Impairment

The pharmacokinetics of ospemifene has not been studied in women with severe hepatic impairment (Child-Pugh Class C); therefore, do not use OSPHENA in women with severe hepatic impairment [see Warnings and Precautions (5.3), and Clinical Pharmacology (12.3)].

No clinically important pharmacokinetic differences with OSPHENA were observed between women with mild to moderate hepatic impairment and healthy women [see Clinical Pharmacology (12.3)].

No dose adjustment of OSPHENA is required in women with mild (Child-Pugh Class A) or moderate (Child-Pugh Class B) hepatic impairment.

11 DESCRIPTION

OSPHENA is an estrogen agonist/antagonist. OSPHENA is not a hormone. The chemical structure of ospemifene is shown in Figure 1.

Figure 1: Chemical Structure

The chemical designation is Z-2-[4-(4-chloro-1,2-diphenylbut-1-enyl)phenoxy]ethanol, and has the empirical formula C24H23ClO2, which corresponds to a molecular weight of 378.9. Ospemifene is a white to off-white crystalline powder that is insoluble in water and soluble in ethanol.

Each OSPHENA tablet contains 60 mg of ospemifene. Inactive ingredients include colloidal silicon dioxide, hypromellose, lactose monohydrate, magnesium stearate, mannitol, microcrystalline cellulose, polyethylene glycol, povidone, pregelatinized starch, sodium starch glycolate, titanium dioxide, and triacetin.

12 CLINICAL PHARMACOLOGY

12.1 Mechanism of Action

OSPHENA is an estrogen receptor agonist/antagonist with tissue selective effects. Its biological actions are mediated through binding to estrogen receptors. This binding results in activation of estrogenic pathways in some tissues (agonism) and blockade of estrogenic pathways in others (antagonism).

12.2 Pharmacodynamics

Generally, a serum estrogen concentration does not predict an individual woman’s therapeutic response to OSPHENA nor her risk for adverse outcomes.

12.3 Pharmacokinetics

Absorption

Following a single oral administration of OSPHENA 60 mg tablet in postmenopausal women under fasted condition, peak median serum concentration was reached at approximately 2 hours (range: 1 to 8 hours) post-dose (see Figure 2). Mean ospemifene Cmaxand AUC0-infwere 533 ng/mL and 4165 ng∙hr/mL, respectively. After a single oral administration of OSPHENA 60 mg tablet in postmenopausal women with a high fat/high calorie (860 kcal) meal, Cmaxwas reached at approximately 2.5 hours (range: 1 to 6 hours) post-dose. Mean ospemifene Cmaxand AUC0-infwere 1198 ng/mL and 7521 ng∙hr/mL, respectively. The absolute bioavailability of ospemifene was not evaluated. Ospemifene exhibits less than dose-proportional pharmacokinetics from 25 to 200 mg with ospemifene capsule formulation. Accumulation of ospemifene with respect to AUC0-infwas approximately 2 after twelve weeks of daily administration. Steady-state was reached after nine days of ospemifene administration.

Figure 2: Mean Serum Concentration Profile of Ospemifene Following a Single Oral Administration of OSPHENA 60 mg Tablet in Postmenopausal Women Under Fed (N=28) and Fasted (N=91) Conditions

Food Effect

In general, food increased the bioavailability of ospemifene by approximately 2-3 fold. In a cross-study comparison, single dose OSPHENA 60 mg tablet administered with a high fat/high calorie meal (860 kcal) in postmenopausal women increased Cmaxand AUC0-infby 2.3- and 1.7-fold, respectively, compared to fasted condition. Elimination half-life and time to maximum concentration (Tmax) were unchanged in the presence of food. In two food effect studies in healthy males using different ospemifene tablet formulations, Cmaxand AUC0-infincreased by 2.3- and 1.8-fold, respectively, with a low fat/low calorie meal (300 kcal) and increased by 3.6- and 2.7-fold, respectively, with a high fat/high calorie meal (860 kcal), compared to fasted condition. OSPHENA should be taken with food [see Dosage and Administration (2.1)].

Distribution

OSPHENA is highly (>99 percent) bound to serum proteins. The apparent volume of distribution is 448 L.

Metabolism

In vitroexperiments with human liver microsomes indicated that ospemifene primarily undergoes metabolism via CYP3A4, CYP2C9, and CYP2C19. The major metabolite was 4-hydroxyospemifene. The apparent total body clearance is 9.16 L/hr using a population approach.

Excretion

The apparent terminal half-life of ospemifene in postmenopausal women is approximately 26 hours. Following an oral administration of ospemifene, approximately 75% and 7% of the dose were excreted in feces and urine, respectively. Less than 0.2% of the ospemifene dose was excreted unchanged in urine.

Use in Specific Populations

Pediatric

The pharmacokinetics of ospemifene in pediatric patients has not been evaluated [see Use in Specific Populations (8.4)].

Geriatric

No differences in ospemifene pharmacokinetics were detected with regard to age (range 40 to 80 years) [see Use in Specific Populations (8.5)].

Race

Race did not have a clinically relevant effect on ospemifene pharmacokinetics.

Renal Impairment

In women with severe renal impairment (CrCL <30 mL/min), the Cmaxand AUC0-inffor ospemifene following a single 60 mg dose administered with a high fat/high calorie meal were lower by 21% and higher by 20%, respectively [see Use in Specific Populations (8.6)].

Hepatic Impairment

In women with mild hepatic impairment (Child-Pugh Class A), the Cmaxand AUC0-inffor ospemifene following a single 60 mg dose administered with a high fat/high calorie meal were lower by 21% and 9.1%, respectively, compared to women with normal hepatic function. In women with moderate hepatic impairment (Child-Pugh Class B), the Cmaxand AUC0-inffor ospemifene following a single 60 mg dose administered with a high fat/high calorie meal were higher by 1% and 29%, respectively, compared to women with normal hepatic function. The effect of severe hepatic impairment on the pharmacokinetics of ospemifene has not been evaluated [see Warnings and Precautions (5.3), and Use in Specific Populations (8.7)].

Drug Interactions

Ospemifene is metabolized primarily by CYP3A4 and CYP2C9. CYP2C19 and other pathways contribute to the metabolism of ospemifene. In order of decreasing potency, ospemifene was suggested to be a weak inhibitor for CYP2B6, CYP2C9, CYP2C19, CYP2C8, CYP2D6, and CYP3A4 in in vitrostudies. Ospemifene is not a significant P-glycoprotein substrate in vitro; no in vivotransporter study was conducted.

Effect of Co-Administered Drugs on the Pharmacokinetics of Ospemifene

Fluconazole (CYP3A4/CYP2C9/CYP2C19 Inhibitor)

Fluconazole (a moderate CYP3A / strong CYP2C9 / moderate CYP2C19 inhibitor) 400 mg was given on Day 1 followed by 200 mg on Days 2 to 5 under fasted condition. On Day 5 approximately one hour after fluconazole administration, ospemifene 60 mg was administered after breakfast (two slices of bread with ham, cheese, a few slices of cucumber and/or tomatoes, and juice). Fluconazole 200 mg was taken for three additional days under fasted condition. Multiple doses of fluconazole in fourteen postmenopausal women increased the Cmaxand AUC0-infof ospemifene by 1.7- and 2.7-fold, respectively [see Drug Interactions (7.2)].

Rifampin (CYP3A4/CYP2C9/CYP2C19 Inducer)

Rifampin 600 mg was given once daily for 5 consecutive days (given at least one hour before or two hours after a meal) in the late afternoon. On Day 6 after an overnight fast, ospemifene 60 mg was administered in the morning after under fed condition (two slices of bread with ham, cheese, a few slices of cucumber and/or tomatoes, and juice). Multiple doses of rifampin 600 mg in twelve postmenopausal women reduced Cmaxand AUC0-infof ospemifene by 51% and 58%, respectively. Rifampin and other inducers of CYP3A4 are expected to decrease the systemic exposure of ospemifene [see Drug Interactions (7.3)].

Ketoconazole (CYP3A4 Inhibitor)

Ketoconazole 400 mg was given once daily for 4 consecutive days after breakfast. On Day 5 after an overnight fast, ketoconazole 400 mg and ospemifene 60 mg were co-administered under fed condition (two slices of bread with ham, cheese, a few slices of cucumber and/or tomatoes, and juice). Ketoconazole administration once daily continued for an additional 3 days (Days 6 to 8). Co-administration of a single 60 mg dose of ospemifene and multiple doses of ketoconazole in twelve postmenopausal women increased Cmaxand AUC0-infby 1.5- and 1.4-fold, respectively [see Drug Interactions (7.4)].

Omeprazole (CYP2C19 Inhibitor)

Omeprazole (a moderate CYP2C19 inhibitor) 40 mg was given for 5 days. On Day 5, approximately one hour after omeprazole administration, ospemifene 60 mg was administered after breakfast (two slices of bread with ham, cheese, a few slices of cucumber and/or tomatoes, and juice). Multiple doses of omeprazole in fourteen postmenopausal women increased Cmaxand AUC0-infby 1.20- and 1.17-fold, respectively.

Effect of Ospemifene on the Pharmacokinetics of the Co-Administered Drug

Warfarin

Ospemifene 60 mg was given after a light breakfast (two slices of bread with ham and cheese, and juice) once daily for 12 days in sixteen postmenopausal women who were determined to be rapid metabolizers of CYP2C9 (CYP2C9*1/*1 or CYP2C9*1/*2). On Day 8, a single dose of warfarin 10 mg and vitamin K 10 mg was administered one hour after a light breakfast. The geometric mean ratio (90% CI) for S-warfarin with and without ospemifene for Cmaxand AUC0-infwas 0.97 (0.92-1.02) and 0.96 (0.91-1.02), respectively. Multiple doses of ospemifene did not significantly affect the pharmacokinetics of a single dose of warfarin. No study was conducted with multiple doses of warfarin.

Omeprazole

Ospemifene 60 mg was administered once daily for 7 days after a light meal in the late afternoon in fourteen postmenopausal women. On Day 8 after an overnight fast, a single 20 mg dose of omeprazole was administered in the morning of at least 10 hrs; ospemifene was not given on Day 8. The geometric mean ratio for the metabolic index (omeprazole/5-hydroxyomeprazole) at the concentration at the 3 hr time point and for AUC0-8hrwas 0.97 with and without ospemifene. It is unclear if ospemifene will affect the pharmacokinetics of drugs metabolized by CYP2C19 due to the significant time gap between ospemifene and omeprazole administration.

Bupropion

Ospemifene 60 mg was administered once daily for seven consecutive days after the evening meal in sixteen postmenopausal women (not homozygous for CYP2B6*6). On Day 8 after an overnight fast, a single 150 mg dose of sustained release bupropion was administered in morning under fasted condition. The geometric mean ratio (90% CI) for bupropion with and without ospemifene for Cmaxand AUC0-infwas 0.82 (0.75-0.91) and 0.81 (0.77-0.86), respectively. The geometric mean ratio (90% CI) for hydroxybupropion, an active metabolite formed via CYP2B6, with and without ospemifene for Cmaxand AUC0-infwas 1.16 (1.09-1.24) and 0.98 (0.92-1.04), respectively.

Midazolam

Ospemifene 60 mg was administered once daily for 14 days in fifteen postmenopausal women. On Day 14, a single 5 mg dose of midazolam (a CYP3A4 substrate) was administered. All doses of midazolam and ospemifene were administered in morning in the fed state (i.e., after a standard breakfast and at the same time every day). The geometric mean ratio (90% CI) for midazolam with and without ospemifene for Cmaxand AUC0-infwas 1.05 (0.95-1.16) and 0.87 (0.82-0.92), respectively.

13 NONCLINICAL TOXICOLOGY

13.1 Carcinogenesis, Mutagenesis, Impairment of Fertility

Carcinogenesis

In a 2-year carcinogenicity study in female mice, ospemifene was orally administered at 100, 400, or 1500 mg/kg/day. No evaluation for carcinogenicity was conducted in male mice. There was significant increase in adrenal subcapsular cell adenomas at 4 and 5 times the human exposure based on AUC, and adrenal cortical tumors at 5 times the human exposure. In the ovary, an increase in sex cord/stromal tumors, tubulostromal tumors, granulosa cell tumors, and luteomas was also seen. These findings occurred at doses 2 to 5 times the human exposure based on AUC and are probably related to estrogenic/antiestrogenic effect of ospemifene in mice.

In a 2-year carcinogenicity study in rats, ospemifene was orally administered at 10, 50, or 300 mg/kg/day. A significant increase in thymomas was recorded for males and thymomas for females at all ospemifene dose levels, or 0.3 to 1.2 times the human exposure based on AUC. In the liver, an increase in hepatocellular tumors was recorded for females at all ospemifene dose levels.

Mutagenesis

Ospemifene was not genotoxic in vitroin the Ames test in strains of Salmonella typhimuriumor at the thymidine kinase (tk) locus of mouse lymphoma L5178Y cells in the absence and in the presence of a metabolic activator system. In in vivotesting, ospemifene was not genotoxic in a standard mouse bone marrow micronucleus test or in a determination of DNA adducts in the liver of rats.

Impairment of Fertility

The effect of ospemifene on fertility was not directly evaluated. In female rats and monkeys, decreases in ovarian and uterine weights, decreased corpora lutea number, increased ovarian cysts, uterine atrophy, and disrupted cycles were observed when given repeated daily oral doses. In male rats, atrophy of the prostate and seminal vesicles was noted. The effects on reproductive organs observed in animals are consistent with the estrogen receptor activity of ospemifene and potential for impairment of fertility.

14 CLINICAL STUDIES

The effectiveness and safety of OSPHENA on moderate to severe symptoms of vulvar and vaginal atrophy in postmenopausal women were examined in four placebo-controlled clinical trials (three 12-week efficacy trials and one 52-week long-term safety trial). In the four placebo-controlled trials, a total of 1100 women received placebo and 1416 women received 60 mg OSPHENA.

Trial 1 was a 12-week, randomized, double-blind, placebo-controlled, parallel-group trial that enrolled 826 generally healthy postmenopausal women between 41 to 81 years of age (mean 59 years of age) who at baseline had ≤5 percent superficial cells on a vaginal smear, a vaginal pH >5.0, and who identified at least one moderate to severe vaginal symptom that was considered the most bothersome to her (vaginal dryness, pain during intercourse [dyspareunia], or vaginal irritation/itching). Treatment groups included 30 mg ospemifene (n=282), 60 mg ospemifene (n=276), and placebo (n=268). All women were assessed for improvement in the mean change from baseline to Week 12 for the co-primary efficacy variables of: most bothersome symptom (MBS) of vulvar and vaginal atrophy (defined as the individual moderate to severe symptom that was identified by the woman as most bothersome at baseline), percentage of vaginal superficial and vaginal parabasal cells on a vaginal smear, and vaginal pH. Following completion of 12-weeks, women with an intact uterus were allowed to enroll in a 40-week double-blind extension study, and women without an intact uterus were allowed to enroll in a 52-week open-label extension study.

Trial 2 was a 12-week, randomized, double-blind, placebo-controlled, parallel-group trial that enrolled 919 generally healthy postmenopausal women between 41 to 79 years of age (mean 59 years of age) who at baseline had ≤5 percent superficial cells on a vaginal smear, a vaginal pH >5.0, and who identified either moderate to severe vaginal dryness (dryness cohort) or moderate to severe dyspareunia (dyspareunia cohort) as most bothersome to her at baseline. Treatment groups included 60 mg ospemifene (n=463) and placebo (n=456). Primary endpoints and study conduct were similar to those in Trial 1.

Trial 3 was a 12-week, randomized, double-blind, placebo-controlled, parallel-group trial that enrolled 631 generally healthy postmenopausal women between 40 and 80 years of age (mean 60 years of age) who at baseline had ≤5 percent superficial cells on a vaginal smear, a vaginal pH >5.0, and had moderate to severe vaginal dryness as the self-reported most bothersome symptom of VVA. Treatment groups included 60 mg ospemifene (n=316) and placebo (n=315). Primary endpoints and study conduct were similar to those in Trials 1 and 2. In Trial 3, 52 healthy postmenopausal women in the 60 mg ospemifene treatment group and 53 in placebo received treatment for up to 52-weeks.

Trial 4 was a 52-week, randomized, double-blind, placebo-controlled, long-term safety trial that enrolled 426 generally healthy postmenopausal women between 49 to 79 years of age (mean 62 years of age) with an intact uterus. Treatment groups included 60 mg ospemifene (n=363) and placebo (n=63).

Effects on Dyspareunia in Postmenopausal Women

In Trials 1 and 2, the modified intent-to-treat population of women treated with ospemifene when compared to placebo demonstrated a statistically significant improvement (least square mean change from baseline to Week 12) in the moderate to severe most bothersome symptom of dyspareunia (Trial 1, p=0.0012 and Trial 2, p<0.0001). See Table 3. A statistically significant increase in the proportion of superficial cells and a corresponding statistically significant decrease in the proportion of parabasal cells on a vaginal smear were also demonstrated (p<0.0001 for both trials). The mean reduction in vaginal pH between baseline and Week 12 was also statistically significant (p<0.0001 for both trials).

Table 3: Week 12 Effects on Dyspareunia (the Woman's Self-Identified Most Bothersome Moderate to Severe Symptom of Vulvar and Vaginal Atrophy at Baseline). Mean Change in Severity at Week 12 with Last Observation Carried Forward (LOCF), Modified Intent-to-Treat Population [The modified intent-to-treat population (mITT) included only women in the ITT population who at baseline met the inclusion criteria of ≤5 percent superficial cells on a vaginal smear, a vaginal pH > 5.0, and who identified moderate or severe dyspareunia as the most bothersome vaginal symptom.]
Trial 1 Results
Most Bothersome Moderate to Severe Symptom at Baseline | OSPHENA (ospemifene) 60 mg (N=110) | Placebo (N=113)
Dyspareunia
Baseline Mean (SD) | 2.7 (0.44) | 2.7 (0.45)
LS Mean Change from Baseline (SE) | -1.4 (0.11) | -0.9 (0.11)
p-value vs. placebo [P-values for dyspareunia were computed using Cochran-Mantel-Haenszel method controlling for study center and uterus status (presence or absence; only in Trial 1).] | 0.0012 | ---
Trial 2 Results
Most Bothersome Moderate to Severe Symptom at Baseline | OSPHENA (ospemifene) 60 mg (N=301) | Placebo (N=297)
Dyspareunia
Baseline Mean (SD) | 2.7 (0.47) | 2.7 (0.47)
LS Mean Change from Baseline (SE) | -1.5 (0.06) | -1.2 (0.07)
p-value vs. placebo | <0.0001 | ---
Definitions: ITT = intent-to-treat; LOCF = last observation carried forward; SD = standard deviation; SE = standard error; LS = least square

Effects on Vaginal Dryness in Postmenopausal Women

All three trials evaluated the most bothersome symptom of vaginal dryness. Trial 2 did not demonstrate a statistically significant improvement in the moderate to severe most bothersome symptom of vaginal dryness. In Trials 1 and 3, the modified intent-to-treat population of women treated with ospemifene when compared to placebo demonstrated a statistically significant improvement in the moderate to severe most bothersome symptom of vaginal dryness (Trial 1, p=0.0136 and Trial 3, p<0.0001). See Table 4. A statistically significant increase in the proportion of superficial cells and a corresponding statistically significant decrease in the proportion of parabasal cells on a vaginal smear were also demonstrated (p<0.0001 for both trials). The mean reduction in vaginal pH between baseline and Week 12 was also statistically significant (p<0.0001 for both trials).

Table 4: Week 12 Effects on Vaginal Dryness (the Woman's Self-Identified Most Bothersome Moderate to Severe Symptom of Vulvar and Vaginal Atrophy at Baseline). Change in Severity at Week 12, Modified Intent-to-Treat Population [The modified intent-to-treat population (mITT) included only women in the ITT population who at baseline met the inclusion criteria of ≤5 percent superficial cells on a vaginal smear, a vaginal pH > 5.0, and who identified moderate or severe vaginal dryness as the most bothersome vaginal symptom.]
Trial 1 Results
Most Bothersome Moderate to Severe Symptom at Baseline | OSPHENA (ospemifene) 60 mg (N=113) | Placebo (N=104)
Vaginal Dryness
Baseline Mean (SD) | 2.5 (0.50) | 2.4 (0.49)
LS Mean Change from Baseline (SE) | -1.3 (0.09) | -0.9 (0.10)
p-value vs. placebo [P-value for vaginal dryness in Trial 1 was computed using Cochran-Mantel-Haenszel method controlling for study center and uterus status (presence or absence), and using LOCF. P-value for vaginal dryness in Trial 3 was computed using a GEE model with terms for treatment group, time, treatment-by-time and study center as fixed effects and baseline value as covariate.] | 0.0136 | ---
Trial 3 Results
Most Bothersome Moderate to Severe Symptom at Baseline | OSPHENA (ospemifene) 60 mg (N=269) | Placebo (N=263)
Vaginal Dryness
Baseline Mean (SD) | 2.6 (0.50) | 2.6 (0.50)
Change from Baseline (SD) | -1.3 (1.00) | -0.9 (0.95)
p-value vs. placebo | < 0.0001 | ---
Definitions: ITT = intent-to-treat; LOCF = last observation carried forward; GEE = generalized estimated equations; SD = standard deviation; SE = standard error; LS = least square

16 HOW SUPPLIED/STORAGE AND HANDLING

16.1 How Supplied

OSPHENA tablets are white to off-white, oval, biconvex, film coated tablets containing 60 mg of ospemifene and engraved with "60" on one side. They are available as follows:

NDC 55494-580-90 | Bottle of 90 tablets
NDC 55494-580-30 | Bottle of 30 tablets

16.2 Storage and Handling

Store at 20ºC to 25ºC (68ºF to 77ºF); excursions permitted to 15ºC to 30ºC (59ºF to 86ºF) [see USP Controlled Room Temperature].

17 PATIENT COUNSELING INFORMATION

Advise women to read the FDA-approved labeling (Patient Information).

Hypersensitivity Reactions

Inform postmenopausal women who have had hypersensitivity reactions to OSPHENA, such as angioedema, urticaria, rash, and pruritus, that they should not use OSPHENA [see Contraindications (4)] .

Vaginal Bleeding

Inform postmenopausal women to report unusual vaginal bleeding to their healthcare providers as soon as possible [see Warnings and Precautions (5.2)] .

Hot Flashes or Flushes

OSPHENA may initiate or increase the occurrence of hot flashes in some women [see Adverse Reactions (6.1)] .

U.S. Patent Nos. 6,245,819 – 9,566,252 – 8,236,861 – 8,470,890 – 8,772,353 – 9,241,915 – 9,855,224 – 8,642,079

PATIENT INFORMATION
OSPHENA®(os fee' nah)
(ospemifene)
tablets, for oral use

Read this Patient Information before you start taking OSPHENA and each time you get a refill. There may be new information. This information does not take the place of talking to your healthcare provider about your medical condition or your treatment.

What is the most important information I should know about OSPHENA?

- OSPHENA is a medicine that works like estrogen in the lining of the uterus (womb) but can work differently in other parts of the body.
- OSPHENA may increase your chance of getting cancer of the lining of the uterus (womb). Vaginal bleeding after menopause may be a warning sign of cancer of the lining of the uterus (womb). Your healthcare provider should check any unusual vaginal bleeding to find out the cause. Tell your healthcare provider right away if you have any unusual vaginal bleeding while you are taking OSPHENA.
- OSPHENA may increase your chance of getting strokes and blood clots.

What is OSPHENA?

- OSPHENA is a prescription medicine that contains ospemifene.
- OSPHENA is used after menopause for women with or without a uterus to treat:
  - Moderate to severe pain during sexual intercourse due to changes in and around your vagina.
  - Moderate to severe vaginal dryness due to changes in and around your vagina.

Who should not take OSPHENA?
Do not start taking OSPHENA if you:

- have unusual vaginal bleeding.Vaginal bleeding after menopause may be a warning sign of cancer of the lining of the uterus (womb). Your healthcare provider should check any unusual vaginal bleeding to find out the cause.
- currently have or have had certain cancers. If you have or have had cancer, talk with your healthcare provider about whether you should take OSPHENA.
- currently have or have had blood clots.
- had a stroke or heart attack.
- are allergic to ospemifene or any of the ingredients in OSPHENA.Allergic reaction to OSPHENA can include swelling of the face or tongue (angioedema), hives (urticaria), rash, and itching (pruritus). See the end of this Patient Information leaflet for a complete list of ingredients in OSPHENA.
- are pregnant or plan to become pregnant. OSPHENA is not for pregnant women.

What should I tell my healthcare provider before taking OSPHENA?
Before you take OSPHENA, tell your healthcare provider about all of your medical conditions, including if you:

- have any unusual vaginal bleeding.
- have or have had certain cancers. See " Who should not take OSPHENA?"
- have liver problems. You should not use OSPHENA if you have certain liver problems.
- are going to have surgery or will be on bed rest. Your healthcare provider will let you know if you need to stop taking OSPHENA.
- are breastfeeding or plan to breastfeed. It is not known if OSPHENA can pass into your breast milk.

Tell your healthcare provider about all medicines you take, including prescription and over-the-counter medicines, vitamins, and herbal supplements. Some medicines may affect how OSPHENA works. OSPHENA may also affect how other medicines work.
Know the medicines you take. Keep a list of your medicines and show it to your healthcare provider and pharmacist each time you get a new medicine.

How should I take OSPHENA?

- Take OSPHENA exactly how your healthcare provider tells you to take it.
- Take 1 OSPHENA tablet by mouth each day with food.
- You and your healthcare provider should talk regularly about the dose of OSPHENA you are taking and whether or not you still need treatment with OSPHENA.

What are the possible side effects of OSPHENA?
OSPHENA may cause serious side effects, including:

- See " What is the most important information I should know about OSPHENA?"

Serious, but less common side effects include:

- stroke

- blood clots

- cancer of the lining of the uterus (womb)

Call your healthcare provider right away if you get any of the following warning signs or any other unusual symptoms that concern you:

- unusual vaginal bleeding
- changes in vision or speech
- sudden new severe headaches
- pain in your chest or legs with or without shortness of breath, weakness and fatigue

Less serious, but common side effects include:

- hot flushes (also known as hot flashes)
- vaginal discharge
- muscle spasms
- headache

- excessive sweating (hyperhidrosis)
- heavy vaginal bleeding (vaginal hemorrhage)
- night sweats

These are not all the possible side effects of OSPHENA. For more information, ask your healthcare provider or pharmacist. Tell your healthcare provider about any side effects that bother you or do not go away.
Call your doctor for medical advice about side effects. You may report side effects to FDA at 1-800-FDA-1088.
What can I do to lower my chances of a serious side effect with OSPHENA?

- Talk with your healthcare provider regularly about whether you should continue taking OSPHENA.
- See your healthcare provider right away if you get vaginal bleeding while taking OSPHENA.
- Have a pelvic exam, breast exam, and mammogram (breast X-ray) every year unless your healthcare provider tells you something else.
- If members of your family have had breast cancer or if you have ever had breast lumps or an abnormal mammogram (breast X-ray), you may need to have breast exams more often.
- If you have high blood pressure, high cholesterol, diabetes, are overweight, or use tobacco, you may have a higher chance of getting heart disease. Ask your healthcare provider for ways to lower your chances of getting heart disease.
- Tell your healthcare provider if you are going to have surgery or will be on bed rest.

How should I store OSPHENA?

- Store OSPHENA at room temperature between 68°F to 77°F (20°C to 25°C).

Keep OSPHENA and all medicines out of the reach of children.

General information about the safe and effective use of OSPHENA.
Medicines are sometimes prescribed for purposes other than those listed in a Patient Information leaflet. Do not take OSPHENA for a condition for which it was not prescribed. Do not give OSPHENA to other people, even if they have the same symptoms you have. It may harm them.
This Patient Information leaflet summarizes the most important information about OSPHENA. If you would like more information, talk with your healthcare provider or pharmacist. You can ask your healthcare provider or pharmacist for information about OSPHENA that is written for health professionals.

What are the ingredients in OSPHENA?
Active Ingredient : ospemifene.
Inactive Ingredients: colloidal silicon dioxide, hypromellose, lactose monohydrate, magnesium stearate, mannitol, microcrystalline cellulose, polyethylene glycol, povidone, pregelatinized starch, sodium starch glycolate, titanium dioxide, and triacetin.
Distributed by: Duchesnay USA, Inc.
Princeton, NJ 08540
Made in UK
For more information, go to www.osphena.com or call Duchesnay Inc. at 1-855-OSPHENA (1-855-677-4362).

This Patient Information has been approved by the U.S. Food and Drug Administration

Revised: 02/2025

PRINCIPAL DISPLAY PANEL - 60 mg Tablet Bottle Label

NDC 55494-580-90
90 Tablets

Osphena®
(ospemifene) tablets
60 mg

For oral use only

DUCHESNAY
Rx only